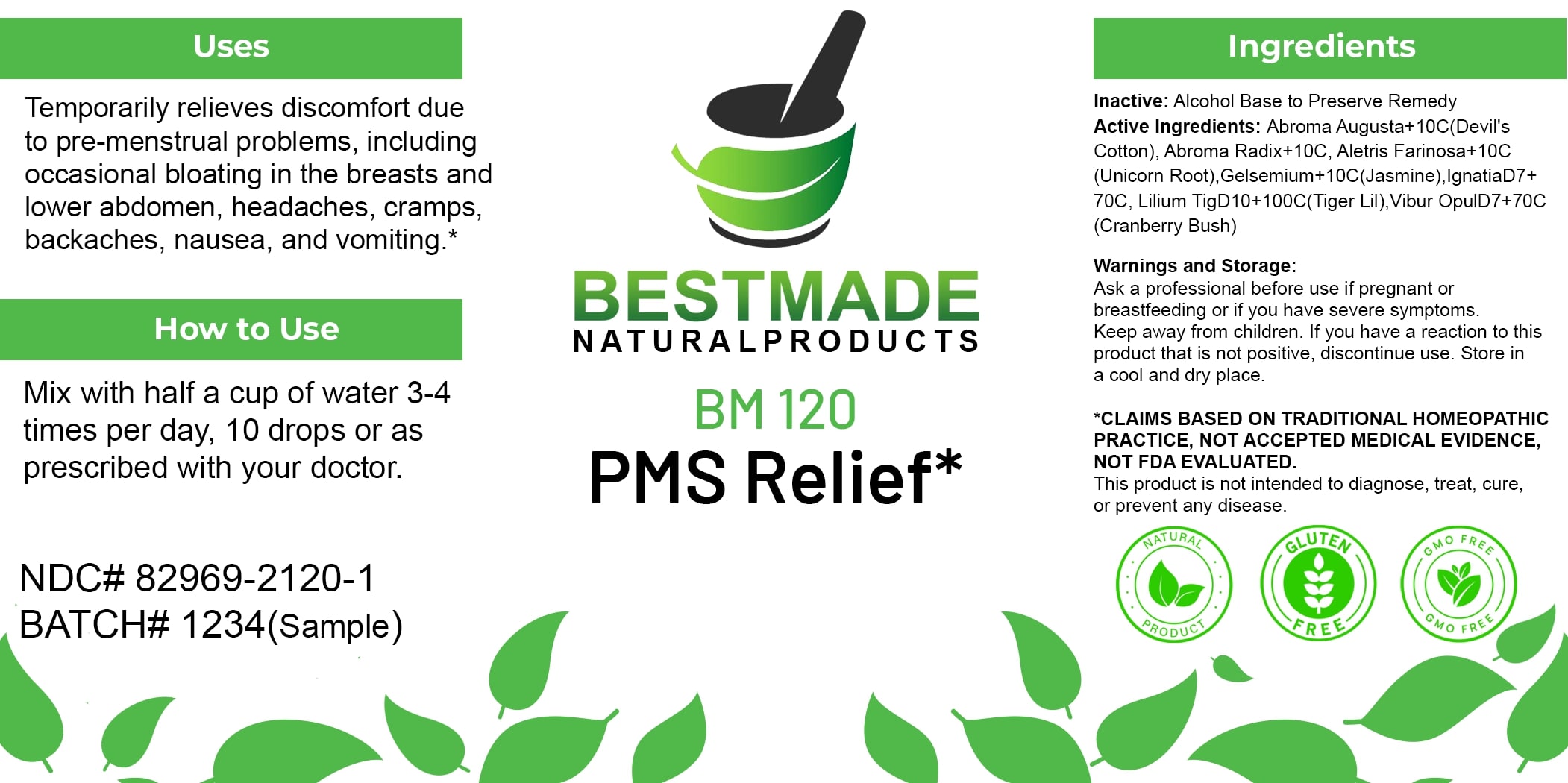 DRUG LABEL: Bestmade Natural Products BM120
NDC: 82969-2120 | Form: LIQUID
Manufacturer: Bestmade Natural Products
Category: homeopathic | Type: HUMAN OTC DRUG LABEL
Date: 20250207

ACTIVE INGREDIENTS: LILIUM LANCIFOLIUM WHOLE FLOWERING 30 [hp_C]/30 [hp_C]; ABROMA AUGUSTUM ROOT 30 [hp_C]/30 [hp_C]; VIBURNUM OPULUS BARK 30 [hp_C]/30 [hp_C]; GELSEMIUM SEMPERVIRENS ROOT 30 [hp_C]/30 [hp_C]; STRYCHNOS IGNATII SEED 30 [hp_C]/30 [hp_C]; ALETRIS FARINOSA ROOT 30 [hp_C]/30 [hp_C]; ABROMA AUGUSTUM WHOLE 30 [hp_C]/30 [hp_C]
INACTIVE INGREDIENTS: ALCOHOL 30 [hp_C]/30 [hp_C]

BM120

DOSAGE AND ADMINISTRATION

How to Use

Mix with half a cup of water 3-4 times per day, 10 drops or as prescribed with your doctor.

INACTIVE INGREDIENT

Ingredients

Inactive: Alcohol Base to Preserve Remedy

ACTIVE INGREDIENT

Active Ingredients: Abroma Augusta+10C(Devil's Cotton), Abroma Radix+10C, Aletris Farinosa+10C (Unicorn Root), Gelsemium+10C(Jasmine), IgnatiaD7+ 70C, Lilium TigD10+100C(Tiger Lily), Vibur OpulD7+70C (Cranberry Bush)

Uses

Temporarily relieves discomfort due to pre-menstrual problems, including occasional bloating in the breasts and lower abdomen, headaches, cramps, backaches, nausea, and vomiting.*

*CLAIMS BASED ON TRADITIONAL HOMEOPATHIC PRACTICE, NOT ACCEPTED MEDICAL EVIDENCE. NOT FDA EVALUATED.

This product is not intended to diagnose, treat, cure, or prevent any disease.

Uses

Temporarily relieves discomfort due to pre-menstrual problems, including occasional bloating in the breasts and lower abdomen, headaches, cramps, backaches, nausea, and vomiting.*

*CLAIMS BASED ON TRADITIONAL HOMEOPATHIC PRACTICE, NOT ACCEPTED MEDICAL EVIDENCE. NOT FDA EVALUATED.

This product is not intended to diagnose, treat, cure, or prevent any disease.

KEEP OUT OF REACH OF CHILDREN

Warnings and Storage:

Ask a professional before use if pregnant or breastfeeding or if you have severe symptoms. Keep away from children. If you have a reaction to this product that is not positive, discontinue use. Store in a cool and dry place.

Warnings and Storage:

Ask a professional before use if pregnant or breastfeeding or if you have severe symptoms. Keep away from children. If you have a reaction to this product that is not positive, discontinue use. Store in a cool and dry place.

*CLAIMS BASED ON TRADITIONAL HOMEOPATHIC PRACTICE, NOT ACCEPTED MEDICAL EVIDENCE. NOT FDA EVALUATED.

This product is not intended to diagnose, treat, cure, or prevent any disease.

Entire package label